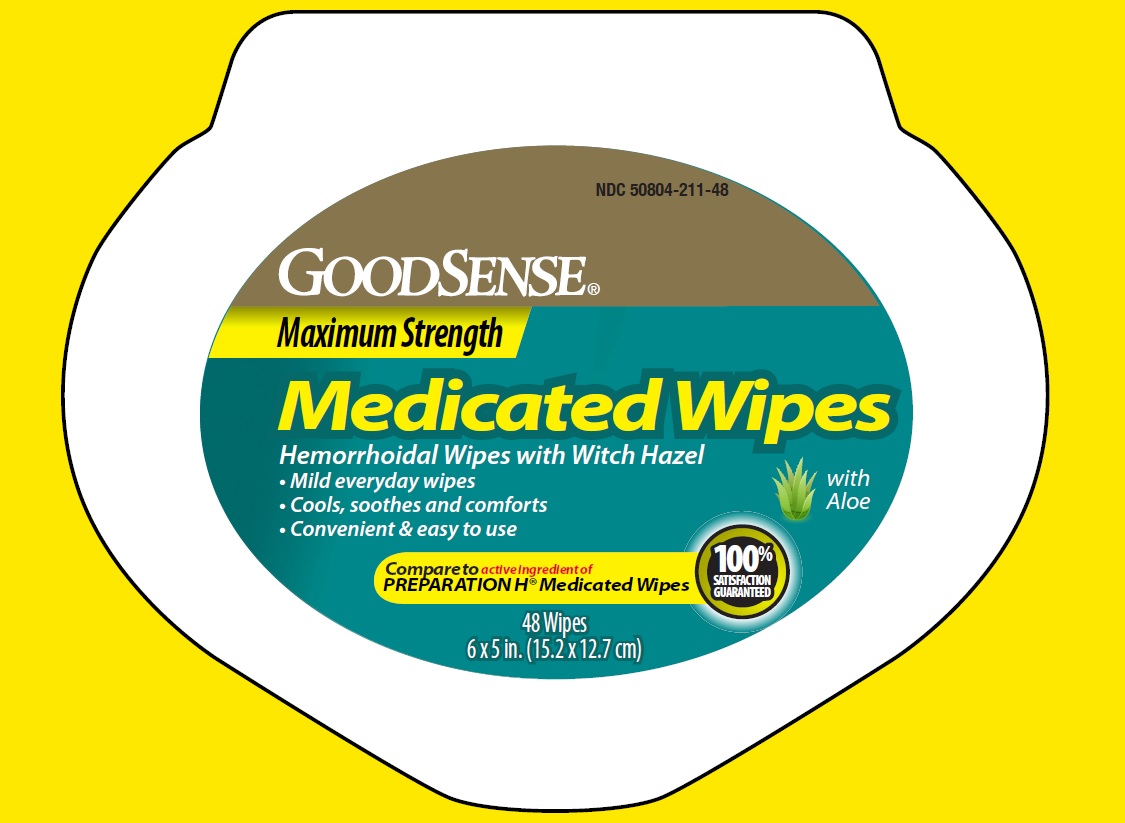 DRUG LABEL: GOODSENSE Maximum Strength Medicated
NDC: 50804-211 | Form: CLOTH
Manufacturer: GEISS, DESTIN & DUNN, INC
Category: otc | Type: HUMAN OTC DRUG LABEL
Date: 20251205

ACTIVE INGREDIENTS: WITCH HAZEL 50 g/100 g
INACTIVE INGREDIENTS: ALCOHOL; ALOE; CITRIC ACID MONOHYDRATE; DECYL GLUCOSIDE; GLYCERIN; PHENOXYETHANOL; POTASSIUM SORBATE; PROPYLENE GLYCOL; SODIUM BENZOATE; WATER

GOODSENSE Maximum Strength Medicated wipes

Active Ingredient

Witch hazel 50%

Purpose

Astringent

Uses

- helps relieve the local itching and discomfort associated with hemorrhoids
- temporary relief of irritation and burning.
- aids in protecting irritated anorectal areas.

Warnings

For external use only.

When using this product

- do not exceed the recommended daily dosage unless directed by a doctor
- do not put this product into the rectum by using fingers or any mechanical device or applicator.

Stop use and ask a doctor if

- bleeding occurs
- condition worsens or does not improve within 7 days

Keep out of reach of children

If swallowed, get medical help or contact a Poison Control Center right away.(1-800-222-1222)

Directions

- adult: unfold wipe and cleanse the area by gently wiping, patting or blotting. If necessary, repeat until all matter is removed from the area.
- use up to 6 times daily or after each bowel movement and before applying hemorrhoidal treatments, and then discard
- children under 12 years of age:Consult a doctor
- Dispose of wipe in trash.
- do not flush

Other information

- store at room temperature 20-25°C (68-77°F)
- for vaginal care - cleanse the area by gently wiping, patting, or blotting. Repeat as needed.
- for use as moist compress - if necessary, first cleanse the area as previously described. Fold wipe to desire size and place in contact with tissue for a soothing and cooling effect. Leave in place for 15 minutes and repeat as needed.

Inactive Ingredients

Alcohol, Aloe, citric acid, Decyl Glucoside, Glycerin, Phenoxyethanol, Potassium Sorbate, Propylene Glycol, Sodium Benzoate, Water.

Principal Display Panel

NDC 50804-211-48

GOODSENSE Maximum Strength

Medicated Wipes with Aloe

Hemorrhoidal Wipes with Witch Hazel

- Mild everyday wipes
- Cools, Soothes and Cofmorts
- Convenient, Easy to use, Flushable Wipes

Compare to active ingredients of PREPARATION H Medicated Wipes

100% satisfaction Guaranteed

48 Wipes

6 X 5 in. (15.2 X12.7 cm)